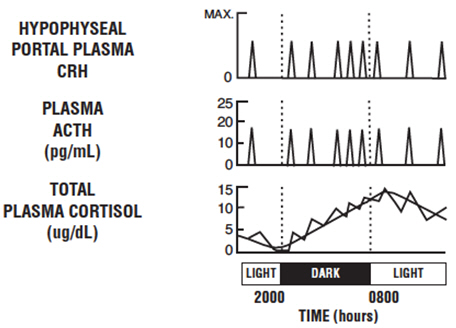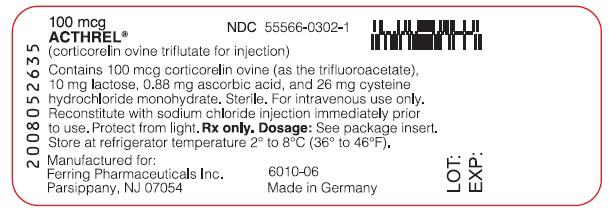 DRUG LABEL: Acthrel
NDC: 55566-0302 | Form: INJECTION, POWDER, LYOPHILIZED, FOR SOLUTION
Manufacturer: Ferring Pharmaceuticals Inc.
Category: prescription | Type: HUMAN PRESCRIPTION DRUG LABEL
Date: 20211112

ACTIVE INGREDIENTS: CORTICORELIN OVINE TRIFLUTATE 100 ug/2 mL
INACTIVE INGREDIENTS: ASCORBIC ACID 0.88 mg/2 mL; LACTOSE, UNSPECIFIED FORM; CYSTEINE HYDROCHLORIDE

ACTHREL ®
(corticorelin ovine triflutate for injection)

For intravenous injection only
DIAGNOSTIC USE ONLY

DESCRIPTION

ACTHREL® (corticorelin ovine triflutate for injection) is a sterile, nonpyrogenic, lyophilized white cake powder, containing corticorelin ovine triflutate, a trifluoroacetate salt of a synthetic peptide that is used for the determination of pituitary corticotroph responsiveness. Corticorelin ovine has an amino acid sequence identical to ovine corticotropin-releasing hormone (oCRH). Corticorelin ovine is an analogue of the naturally occurring human CRH (hCRH) peptide. Both peptides are potent stimulators of adrenocorticotropic hormone (ACTH) release from the anterior pituitary. ACTH stimulates cortisol production from the adrenal cortex. The structural formula for corticorelin ovine triflutate is described below:

Ser-Gin-Glu-Pro-Pro-Ile-Ser-Leu-Asp-Leu-Thr-Phe-His-Leu-Leu-Arg-Glu-Val-Leu-Glu-Met-Thr-Lys-Ala-Asp-Gin-Leu-Ala-Gln-Gln-Ala-His-Ser-Asn-Arg-Lys-Leu-Leu-Asp-Ile-Ala-NH2∙xCF2COOH

whereas x=4 - 8.

The empirical formula of corticorelin ovine is C205H339N59O63S with a molecular weight of 4670.35 Daltons.

ACTHREL® for injection is available in vials containing 100 mcg corticorelin ovine (as the trifluoroacetate), 0.88 mg ascorbic acid, 10 mg lactose, and 26 mg cysteine hydrochloride monohydrate. Trace amounts of chloride ion may be present from the manufacturing process. The preparation is intended for intravenous administration.

CLINICAL PHARMACOLOGY

Pharmacodynamics

In normal subjects, intravenous administration of corticorelin results in a rapid and sustained increase of plasma ACTH levels and a near parallel increase of plasma cortisol. In addition, intravenous administration of corticorelin to normal subjects causes a concomitant and prolonged release of the related proopiomelanocortin peptides β- and γ-lipotropins (β -and γ-LPH) and β-endorphin (β -END). A number of dose-response studies have been performed on normal subjects using a range of corticorelin doses. In one study, doses of corticorelin ranging from 0.001 to 30 mcg/kg body weight were administered to 29 healthy volunteers. Blood samples were taken over a 2-hour period for determination of plasma ACTH and cortisol concentrations. There was a direct dose-dependent relationship that was more pronounced for ACTH than for cortisol. The threshold dose was 0.03 mcg/kg, the half-maximal dose was 0.3-1.0 mcg/kg and the maximally effective dose was 3-10 mcg/kg.

Plasma ACTH levels in normal subjects increased 2 minutes after injection of corticorelin doses of ≥0.3 mcg/kg and reached peak levels after 10-15 minutes. Plasma cortisol levels increased within 10 minutes and reached peak levels at 30 to 60 minutes. As the dose of corticorelin was increased, the rises in plasma ACTH and cortisol were more sustained, showing a biphasic response with a second lower peak at 2-3 hours after injection. Similar results were found in another study using 0.3, 3.0, and 30 mcg/kg doses. The duration of mean plasma ACTH increase after injection of 0.3, 3.0, and 30 mcg/kg was 4, 7, and 8 hours, respectively. The effect on plasma cortisol was similar, but more prolonged. Because there are differences in basal levels and peak response levels following a.m. or p.m. administration, it is recommended that subsequent evaluations in the same patient using the corticorelin stimulation test be carried out at the same time of day as the original evaluation.

Baseline ACTH and cortisol levels are usually higher in the morning. Pooled ACTH values from normal unstressed subjects (n=119) were 25 ± 7 pg/mL in the a.m. and 10 ± 3 in the p.m.; similar pooled cortisol values (n=170) were 11 ± 3 mcg/dL in the a.m. and 4 ± 2 mcg/dL in the p.m. The normal unstressed person has about seven to ten secretory episodes of ACTH each day. Most of them occur in the early morning hours and are responsible for the morning plasma cortisol surge. The following figure shows the daily circadian rhythm of ACTH and cortisol secretions in a normal unstressed person. Insulin, plasma renin activity, prolactin, and growth hormone release are not affected by corticorelin administration in humans.

Continuous 24-hour infusion of corticorelin (0.5, 1.0, and 3.0 mcg/kg/hr) increased plasma ACTH concentrations to a plateau of 15-20 pg/mL by the third hour and urinary-free cortisol reaches 173 ± 43 mcg/dL by 24 hours, comparable to those levels observed in patients with major depression, but less than levels noted in Cushing's disease. Continuous infusion did not abolish the circadian rhythm of plasma ACTH and cortisol, but did appear to desensitize the corticotroph. Intermittent doses of corticorelin (25 mcg every 4 hours for 72 hours), however, continued to elicit the expected ACTH and cortisol responses.

Intravenous administration of 1 mcg/kg corticorelin in combination with 10 pressor units intramuscular vasopressin had a synergistic effect on ACTH and a less marked synergistic effect on cortisol secretion.

The basal and peak response levels of ACTH and cortisol to a 1 mcg/kg or 100 mcg dose of corticorelin administered to normal volunteers in the morning and the evening are given below. These values were obtained by combining the results from 9 clinical trials conducted in the a.m. and 4 clinical trials conducted in the p.m.

The following table is to be used only as a general guide.

Basal Concentrations and Peak Responses of ACTH and Cortisol in Normal Subjects after 1 mcg/kg or 100 mcg of ACTHREL®
Time of Day | No. of Subjects | ACTH Concentration mean (range) pg/mL |  | Cortisol Concentration mean (range) mcg/dL
Time of Day | No. of Subjects | Basal | Peak | Basal | Peak
a.m. | 143 | 28 (16-65) | 68 (39-114) | 11 (8-13) | 21 (17-25)
p.m. | 70 | 9 (8-13) | 30 (25-42) | 4 (2-6) | 16 (15-18)

Pharmacokinetics

Following a single intravenous injection of 1 mcg/kg of corticorelin to normal men, the disappearance of immunoreactive corticorelin (IR-corticorelin) from plasma follows a biexponential decay curve. Plasma half-lives for IR-corticorelin are 11.6 ± 1.5 minutes (mean ± SE) for the fast component and 73 ± 8 minutes for the slow component. The mean volume of distribution for IR-corticorelin is 6.2 ± 0.5 L with an approximate metabolic clearance rate of 95 ± 11 L/m^2/day. Graded intravenous doses of corticorelin (0.01, 0.03, 0.1, 0.3, 1, 3, 10, 30 mcg/kg) produced a linear increase in plasma IR-corticorelin. Corticorelin does not appear to be bound specifically by a circulating plasma protein.

INDICATIONS AND USAGE

ACTHREL® is indicated for use in differentiating pituitary and ectopic production of ACTH in patients with ACTH-dependent Cushing's syndrome.

Differential Diagnosis

There are two forms of Cushing's syndrome:

1. ACTH-dependent (83%), in which hypercortisolism is due either to pituitary hypersecretion of ACTH (Cushing's disease) resulting from an adenoma (40%, usually microadenomas) or nonadenomatous hyperplasia, possibly of hypothalamic origin (28%), or to hypercortisolism that is secondary to ectopic secretion of ACTH (15%) and,
2. ACTH- independent (17%), in which hypercortisolism is due to autonomous cortisol secretion by an adrenal tumor (9% adenomas, 8% carcinomas).

After the establishment of hypercortisolism consistent with the presence of Cushing's syndrome, and following the elimination of autonomous adrenal hyperfunction as its cause, the corticorelin test is used to aid in establishing the source of excessive ACTH secretion.

The corticorelin stimulation test helps to differentiate between the etiologies of ACTH-dependent hypercortisolism as follows:

- High basal plasma ACTH plus high basal plasma cortisol (20 - 40 mcg/dL). ACTHREL® injection (1 mcg/kg) results in:
  1. Increased plasma ACTH levels
  2. Increased plasma cortisol levels
    Diagnosis: Cushing's disease (ACTH of pituitary origin)
- High basal plasma ACTH (may be very high) plus high basal plasma cortisol (20 - 40 mcg/dL). ACTHREL® injection (1 mcg/kg) results in:
  1. Little or no response of plasma ACTH levels
  2. Little or no response of plasma cortisol levels
  Diagnosis: Ectopic ACTH syndrome

Test Methodology

To evaluate the status of the pituitary-adrenal axis in the differentiation of a pituitary source from an ectopic source of excessive ACTH secretion, a corticorelin test procedure requires a minimum of five blood samples.

Procedure

1. Venous blood samples should be drawn 15 minutes before and immediately prior to ACTHREL® administration. The ACTH baseline is obtained by averaging the values of the two samples.
2. Administer ACTHREL® as an intravenous infusion over a 30 to 60- second interval at a dose of 1 mcg/kg body weight. Higher doses are not recommended (see PRECAUTIONS and ADVERSE REACTIONS).
3. Draw venous blood samples at 15, 30, and 60 minutes after administration.
4. Blood samples should be handled as recommended by the laboratory that will determine their ACTH content. It is extremely important to recognize that the reliability of the ACTHREL® test is directly related to the inter-assay and intra-assay variability of the laboratory performing the assay.

Cortisol determinations may be performed on the same blood samples for the same time points as outlined above. The blood sample handling precautions noted for ACTH should be followed for cortisol.

Interpretation of Test Results

The interpretation of the ACTH and cortisol responses following ACTHREL® administration requires a knowledge of the clinical status of the individual patient, understanding of hypothalamic-pituitary-adrenal physiology, and familiarity with the normal hormonal ranges and the standards used by the laboratory that performs the ACTH and cortisol assays.

Cushing's Disease

The results of challenge with corticorelin injection have been reported in approximately 300 patients with Cushing's disease. Although the ACTH and cortisol responses were variable, a hyper-response to corticorelin was seen in a majority of patients, despite high basal cortisol levels. This response pattern indicates an impairment of the negative feedback of cortisol on the pituitary. Patients with pituitary-dependent Cushing's disease tested with corticorelin do not show the negative correlation between basal and stimulated levels of ACTH and cortisol that is found in normal subjects. A positive correlation between basal ACTH levels and maximum ACTH increments after corticorelin administration has been found in Cushing's disease patients.

Ectopic ACTH Secretion

Patients with Cushing's syndrome due to ectopic ACTH secretion (N=32) were found to have very high basal levels of ACTH and cortisol, which were not further stimulated by corticorelin. However, there have been rare instances of patients with ectopic sources of ACTH that have responded to the corticorelin test.

SUMMARY OF ACTH RESPONSES IN PATIENTS WITH HIGH BASAL CORTISOL
 | High ACTH Response | Low ACTH Response
High Basal ACTH | Cushing's Disease | Ectopic ACTH Secretion

CUSHING'S DISEASE ACTH RESPONSES
(mean of 181 patients)
Basal ACTH 63 ± 72 pg/mL (mean ± SD)
Peak ACTH 189 ± 262 pg/mL (mean ± SD)
Mean of individual change from baseline + 227%

ECTOPIC ACTH SECRETION RESPONSES
(mean for 31 patients)
Basal ACTH 266 ± 464 pg/mL (mean ± SD)
Peak ACTH 276 ± 466 pg/mL (mean ± SD)
Mean of individual change from baseline + 15%

False negative responses to the corticorelin test in Cushing's disease patients occur approximately 5 to 10% of the time, which may lead the clinician to an incorrect diagnosis of ectopic production of ACTH at that frequency (see INDICATIONS AND USAGE, Differential Diagnosis).

CONTRAINDICATIONS

ACTHREL is contraindicated in patients with a history of a hypersensitivity reaction to ovine corticorelin or any of its excipients.

PRECAUTIONS

General

The severity of adverse effects to a corticorelin injection appear to be dose-dependent. Dosages above 1 mcg/kg are not recommended. While few adverse effects have been observed at the 1 mcg/kg or 100 mcg dose, higher doses have been associated with transient tachycardia, decreased blood pressure, loss of consciousness, and asystole (see ADVERSE REACTIONS). These symptoms can be substantially reduced by administering the drug as a 30-second intravenous infusion instead of a bolus injection. At a dose of 200 mcg corticorelin, 4 of 60 volunteers and patients with disturbances of the hypothalamic-pituitary-adrenal (HPA) axis were reported to have had decreased blood pressures. One patient had a severe hypotensive reaction with asystole. Three other patients had an "absence-like" loss of consciousness lasting approximately 5 minutes. In subsequent investigations by the same researchers over a 3-year period using 100 mcg of corticorelin, one patient in approximately 150 to 200 experienced a severe drop in blood pressure and loss of sinus rhythm after receiving 55 mcg of corticorelin, which may have been due to interaction with heparin (see PRECAUTIONS - Drug Interactions).

Hypersensitivity

Hypersensitivity reactions have been reported in patients receiving ACTHREL. Reactions included urticaria, flushing of the face, neck and upper chest; dyspnea, wheezing, urticaria and angioedema involving tongue, lip and facial swelling (see ADVERSE REACTIONS). Should a hypersensitivity reaction occur, discontinue ACTHREL, monitor and treat if indicated.

Drug Interactions

The plasma ACTH response to corticorelin injection is inhibited or blunted in normal subjects pretreated with dexamethasone. The use of a heparin solution to maintain i.v. cannula patency during the corticorelin test is not recommended. A possible interaction between corticorelin and heparin may have been responsible for a major hypotensive reaction that occurred after corticorelin administration (see ADVERSE REACTIONS).

Carcinogenesis, Mutagenesis, Impairment of Fertility

Animal studies have not been conducted with corticorelin to evaluate carcinogenic potential, mutagenicity, or effect on fertility.

Pregnancy

Animal reproduction studies have not been conducted with corticorelin. It is also not known whether corticorelin can cause fetal harm when administered to a pregnant woman or can affect reproductive capacity. ACTHREL ® should be given to a pregnant woman only if clearly needed.

Nursing Mothers

It is not known whether corticorelin is secreted in human milk. Because many drugs are excreted in human milk, caution should be exercised when ACTHREL® is administered to a nursing woman.

PEDIATRIC USE

Only a few tests have been performed on children. Dosages were 1 mcg/kg body weight. Patient studies have involved only children with multiple hypothalamic and/or pituitary hormone deficiencies, or tumors. Only two studies with normal pediatric subjects have been conducted. No differences in response to the corticorelin test have been reported in the children studied.

ADVERSE REACTIONS

Hypersensitivity reactions have been reported with 1 mcg/kg or 100 mcg/patient and include flushing of the face, neck, and upper chest; dyspnea, wheezing, urticaria, and angioedema (involving tongue, lip and facial swelling). Subjects have also reported an urge to take a deep breath, which occurs with a timing similar to, but less frequently than, that of flushing. Higher doses (>3 mcg/kg) are associated with more prolonged flushing, tachycardia, hypotension, dyspnea, and "chest compression" or tightness. In addition, at doses of >5 mcg/kg, significant increases in heart rate and decreases in blood pressure were observed. The cardiovascular effects occurred 2-3 minutes after injection and lasted for 30-60 minutes. The facial flushing was more prolonged, lasting up to 4 hours in some subjects. All signs and symptoms could be reduced by administering the drug as a 30-second infusion instead of by bolus injection.

Total doses of up to 200 mcg of corticorelin were administered as a bolus injection to 60 men and women, including both healthy normal subjects and patients with endocrine disorders. In most cases, only minor adverse effects, such as transient flushing and feelings of dyspnea, were noted. However, a few patients with disorders of the pituitary-adrenal axis had major symptoms. One patient had a precipitous fall in blood pressure and pulse rate and developed asystole, which required resuscitation. In two patients with Cushing's disease and in one with secondary adrenal insufficiency, an "absence-like" loss of consciousness occurred, which started within a few seconds after injection of corticorelin and lasted from 10 seconds to 5 minutes. This was accompanied by a slight fall in blood pressure. One patient with a well documented seizure diathesis experienced a grand mal epileptic seizure following ACTHREL® administration. The patient had discontinued anti-convulsant therapy the day of the procedure (see PRECAUTIONS - Drug Interactions).

OVERDOSAGE

Symptoms of overdose include severe facial flushing, cardiovascular changes, and dyspnea. In the event of toxic overdose (see ADVERSE REACTIONS), adverse effects should be treated symptomatically.

DOSAGE AND ADMINISTRATION

Dosage

A single intravenous dose of ACTHREL® at 1 mcg/kg is recommended for the testing of pituitary corticotrophin function. A dose of 1 mcg/kg is the lowest dose that produces maximal cortisol responses and significant (though apparently sub-maximal) ACTH responses. Doses above 1 mcg/kg are not recommended (see PRECAUTIONS and ADVERSE REACTIONS).

At a dose of 1 mcg/kg, the ACTH and cortisol responses to ACTHREL® are prolonged and remain elevated for up to 2 hours. The maximum increment in plasma ACTH occurs between 15 and 60 minutes after ACTHREL® administration, whereas the maximum increment in plasma cortisol occurs between 30 and 120 minutes. In a clinical study of 30 normal healthy men, the peak plasma ACTH and cortisol responses to ACTHREL® administration in the early afternoon occurred at 42 ± 29 minutes and 65 ± 26 minutes (average ±SD), respectively. If a repeated evaluation using the corticorelin stimulation test with ACTHREL® is needed, it is recommended that the repeat test be carried out at the same time of day as the original test because there are differences in basal levels and peak response levels following a.m. or p.m. administration to normal humans.

Administration

ACTHREL® is to be reconstituted aseptically with 2 mL of Sodium Chloride injection, USP (0.9% sodium chloride), at the time of use by injecting 2 mL of the saline diluent into the lyophilized drug product cake. To avoid bubble formation, DO NOT SHAKE the vial; instead, roll the vial to dissolve the product. The sterile solution containing 50 mcg corticorelin/mL is then ready for injection by the intravenous route. The dosage to be administered is determined by the patient's weight (1 mcg corticorelin/kg). Some of the adverse effects can be reduced by administering the drug as an infusion over 30 seconds instead of as a bolus injection.

Parenteral drug products should be inspected visually for particulate matter and discoloration prior to administration, whenever solution and container permit.

HOW SUPPLIED

ACTHREL® is supplied as a sterile, nonpyrogenic, lyophilized, white cake containing 100 mcg corticorelin ovine (as the trifluoroacetate), 0.88 mg ascorbic acid, 10 mg lactose, and 26 mg cysteine hydrochloride monohydrate. Trace amounts of chloride ion may be present from the manufacturing process. The package provides a single-dose, rubber-capped, 5 mL, brown-glass vial (NDC 55566-0302-1) containing 100 mcg corticorelin ovine (as the trifluoroacetate). ACTHREL® is stable in the lyophilized form when stored refrigerated at 2°C to 8°C (36°F to 46°F) and protected from light. The reconstituted solution is stable up to 8 hours under refrigerated conditions. Discard unused reconstituted solution.

MANUFACTURED FOR:

FERRING PHARMACEUTICALS INC.
PARSIPPANY, NJ 07054

Origin Germany

Rx only

Rev. 09/2018
XXXXXXXXXX

PRINCIPAL DISPLAY PANEL - 100 mcg Vial Label

100 mcg
ACTHREL®
(corticorelin ovine triflutate for injection)

NDC 55566-0302-1

Contains 100 mcg corticorelin ovine (as the trifluoroacetate),
10 mg lactose, 0.88 mg ascorbic acid, and 26 mg cysteine
hydrochloride monohydrate. Sterile. For intravenous use only.
Reconstitute with sodium chloride injection immediately prior
to use. Protect from light. Rx only. Dosage: See package insert.
Store at refrigerator temperature 2° to 8°C (36° to 46°F).

Manufactured for:
Ferring Pharmaceuticals Inc.
Parsippany, NJ 07054

6010–06
Made in Germany

LOT:
EXP:

2008052635